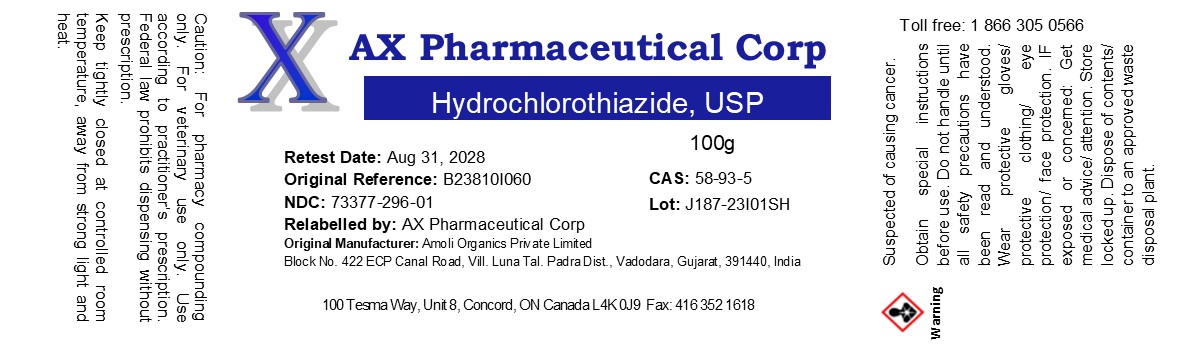 DRUG LABEL: Hydrochlorothiazide
NDC: 73377-296 | Form: POWDER
Manufacturer: AX Pharmaceutical Corp
Category: other | Type: BULK INGREDIENT - ANIMAL DRUG
Date: 20241017

ACTIVE INGREDIENTS: Hydrochlorothiazide 1 g/1 g

Hydrochlorothiazide